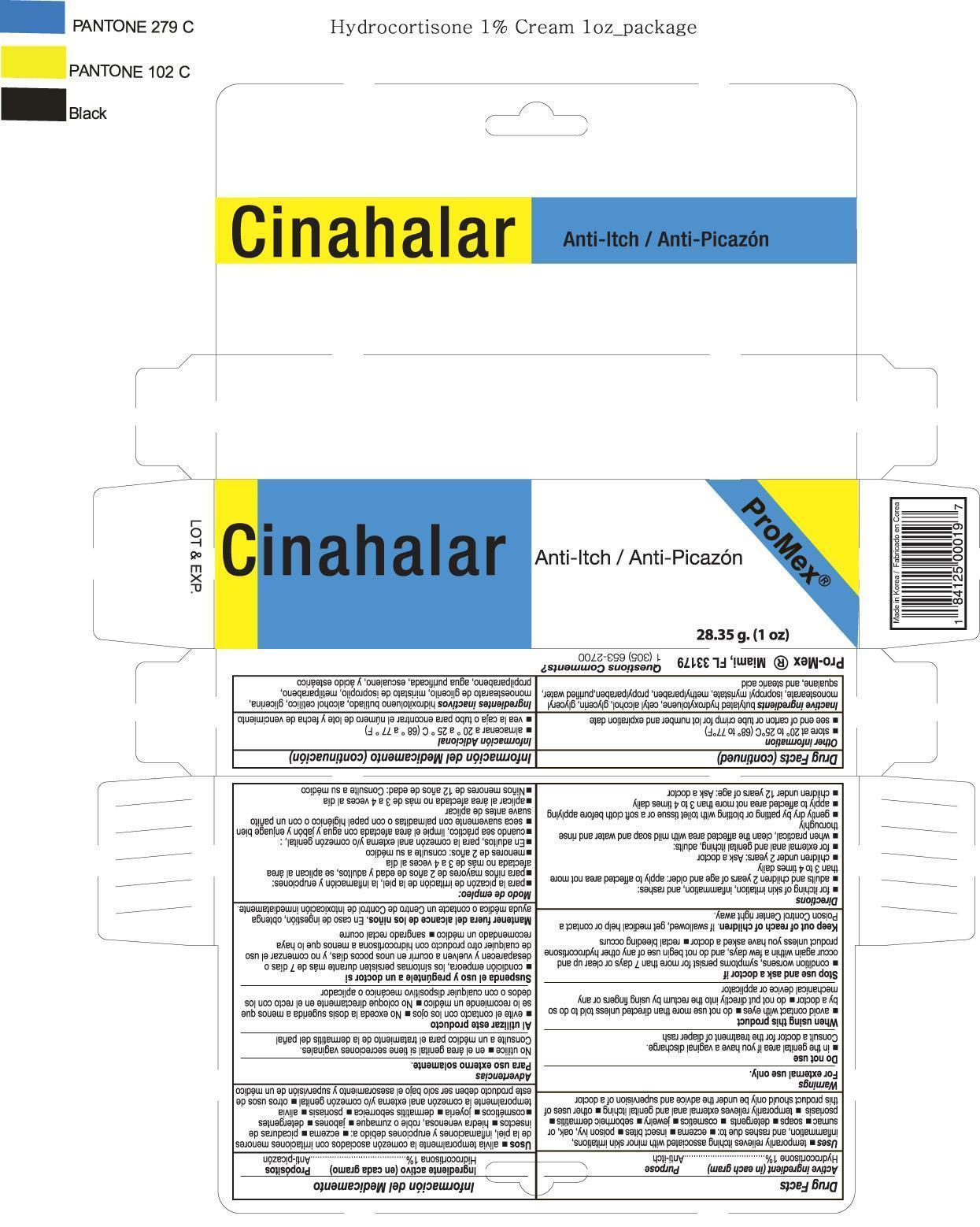 DRUG LABEL: Hydrocortisone
NDC: 58988-0019 | Form: CREAM
Manufacturer: Promex, LLC
Category: otc | Type: HUMAN OTC DRUG LABEL
Date: 20180309

ACTIVE INGREDIENTS: HYDROCORTISONE 1 g/100 g
INACTIVE INGREDIENTS: CETYL ALCOHOL; BUTYLATED HYDROXYTOLUENE; GLYCERIN; GLYCERYL MONOSTEARATE; ISOPROPYL MYRISTATE; METHYLPARABEN; SQUALANE; STEARIC ACID; PROPYLPARABEN; WATER

Drug Facts

Active Ingredient

Hydrocortisone 1%

Purpose

Anti-itch

Uses

- temporarily relieves itching associated with minor sin irritation, inflammation and rashes due to:
- eczema
- insect bites
- poison ivy, oak, or sumac
- soaps
- detergents
- cosmetics
- jewelry
- seborrheic dermatitis
- psoriasis
- temporarily relieves external anal and genital itching
- other uses of this product should only be under the advice and supervision of a doctor

Warnings

For external use only

Do not use

- in the genital area if you have a vaginal discharge.
- Consult a doctor for the treatment of diaper rash

When using this product

- avoid contact with eyes
- do not use more than directed unless told to do so by a doctor
- do not put directly into the rectum by using fingers or any mechanical device or applicator

Stop use and ask a doctor if

- condition worsens, symptoms persist for more than 7 days or clear up and occur again within a few days, and do not begin us of any other hydrocortisone product unless you have asked a doctor
- rectal bleeding occurs

Keep out of reach of children

If swallowed, get medical help or contact a Poison Control right away.

Directions

- for itching of skin irritation, inflammation, and rashes:
- adults and children 2 years of age and older: apply to affected area not more than 3 to 4 times daily
- children under 2 years: Ask a doctor
- for external anal and genital itching, adults:
- when practical, clean the affected area with mild soap and water and rinse thoroughly
- gently dry by patting or blotting with toilet tissue or a soft cloth before applying
- apply to affected area not more than 3 to 4 times daily
- children under 12 years of age: Ask a doctor

Other information

- store at 20 to 25oC (68 to 77oF)

Inactive Ingredient

Butylated hydroxytoluene, Cetyl alcohol, Glycerin, Glyceryl monostearate, Isopropyl myristate, Methylparaben, Propylparaben, Purified water, Squalane and Stearic acid

PACKAGE LABEL

Hydrocortisone